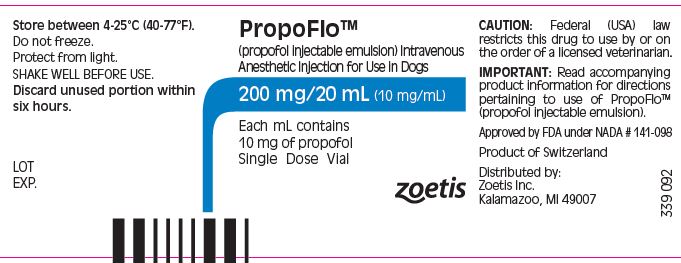 DRUG LABEL: PropoFlo
NDC: 54771-5206 | Form: INJECTION, EMULSION
Manufacturer: Zoetis Inc.
Category: animal | Type: PRESCRIPTION ANIMAL DRUG LABEL
Date: 20230404

ACTIVE INGREDIENTS: PROPOFOL 10 mg/1 mL
INACTIVE INGREDIENTS: SOYBEAN OIL 100 mg/1 mL; GLYCERIN 22.5 mg/1 mL; EGG PHOSPHOLIPIDS 12 mg/1 mL; OLEIC ACID 0.6 mg/1 mL; SODIUM HYDROXIDE

PropoFloTM

For Animal Use Only

PropoFloTM
(propofol injectable emulsion) Intravenous Anesthetic Injection for Use in Dogs.

Fliptop vial. Each mL contains 10 mg propofol.
Shake Well Before Use.

CAUTION

Federal (USA) law restricts this drug to use by or on the order of a licensed veterinarian.

DESCRIPTION

PropoFlo™ Injection is a sterile, nonpyrogenic emulsion containing 10 mg/mL of propofol suitable for intravenous administration. Propofol is chemically described as 2, 6-diisopropylphenol and has a molecular weight of 178.27. Propofol is very slightly soluble in water and is therefore formulated as a white, oil-in-water emulsion. In addition to the active component, propofol, the formulation also contains soybean oil (100 mg/mL), glycerol (22.5 mg/mL), egg lecithin (12 mg/mL), and oleic acid (0.6 mg/mL) with sodium hydroxide to adjust the pH. The propofol emulsion is isotonic and has a pH of 6.0-9.0.

CLINICAL PHARMACOLOGY

Propofol injection is an intravenous sedative hypnotic agent for use in the induction and maintenance of anesthesia. Intravenous injection of propofol in the dog is followed by extensive metabolism of propofol in the liver to inactive conjugates which are excreted in the urine. Elimination from the central compartment occurs rapidly, with an initial elimination phase of less than 10 minutes^1.

Induction of anesthesia will usually be observed within 75-120 seconds after the beginning of propofol administration. The duration of anesthesia following the recommended induction doses averages 6.7 minutes in premedicated and unpremedicated animals.

Recommended maintenance doses for anesthesia in unpremedicated animals, animals premedicated with acepromazine, and animals premedicated with a combination of agents results in anesthesia lasting an average of 3.68, 3.80 and 5.43 minutes, respectively, after each maintenance dose.

Recovery from propofol is rapid; full standing recovery is generally observed within 20 minutes. The use of certain premedicant combinations (e.g., acepromazine/oxymorphone) may result in prolonged recovery. Recovery may be delayed in Sighthounds.

Propofol has been used in association with atropine, glycopyrrolate, acepromazine, xylazine, oxymorphone, halothane and isoflurane. No pharmacological incompatibility has been observed.

INDICATIONS

Propofol is an intravenous anesthetic injection for use in dogs as follows:
1. For induction of anesthesia.
2. For maintenance of general anesthesia for up to 20 minutes.
3. For induction of general anesthesia where maintenance is provided by inhalant anesthetics.

DOSAGE AND ADMINISTRATION

Shake the vial thoroughly before opening.

Parenteral drug products should be inspected visually for particulate matter and discoloration prior to administration, whenever solution and container permit. Propofol is a white stable emulsion; do not use if there is evidence of separation of the phases. Do not use if there is evidence of excessive creaming or aggregation, if large droplets are visible, or if there are other forms of phase separation indicating that the stability of the product has been compromised. Slight creaming, which should disappear after shaking, may be visible upon prolonged standing. Do not use if particulate matter and discoloration are present.

Propofol contains no antimicrobial preservatives. Strict aseptic techniques must always be maintained during handling since the vehicle is capable of supporting the rapid growth of microorganisms. Failure to follow aseptic handling procedures may result in microbial contamination causing fever, infection/sepsis, and/or other life-threatening illness. Do not use if contamination is suspected.

Once propofol has been opened, vial contents should be drawn into sterile syringes; each syringe should be prepared for single patient use only.

Unused product should be discarded within 6 hours.

The emulsion should not be mixed with other therapeutic agents prior to administration. Administer by intravenous injection only.

INDUCTION OF GENERAL ANESTHESIA

For induction, propofol injection should be titrated against the response of the patient over 30-60 seconds or until clinical signs show the onset of anesthesia. Rapid injection of propofol (≤ 5 seconds) may be associated with an increased incidence of apnea^2.

The average propofol induction dose rates for healthy dogs given propofol alone, or when propofol is preceded by a premedicant, are indicated in the table below. This table is for guidance only. The dose and rate should be based upon patient response.

Induction Dosage Guidelines
Preanesthetic | Propofol Induction | Propofol Rate of Administration
 | Dose
 | mg/kg | Seconds | mg/kg/min | mL/kg/min
None | 5.5 | 40 - 60 | 5.5 - 8.3 | 0.55 - 0.83
Acepromazine | 3.7 | 30 - 50 | 4.4 - 7.4 | 0.44 - 0.74
Acepromazine / Oxymorphone | 2.6 | 30 - 50 | 3.1 - 5.2 | 0.31 - 0.52

Propofol doses and rates for the above premedicants were based upon the following average dosages. These doses may be lower than the label directions for their use as a single medication^3,4.

Dose (mg/kg) |  | Routes
Acepromazine | 0.060 | IM, SC, IV
Oxymorphone | 0.090 | IM, SC, IV
Xylazine | 0.33 | IM, SC

The use of these drugs as preanesthetics markedly reduces propofol requirements. As with other sedative hypnotic agents, the amount of opioid and/or α-2 agonist premedication will influence the response of the patient to an induction dose of propofol.

In the presence of premedication, the dose of propofol may be reduced with increasing age of the animal. The dose of propofol should always be titrated against the response of the patient.

During induction, additional low doses of propofol, similar to those used for maintenance with propofol, may be administered to facilitate intubation or the transition to inhalant maintenance anesthesia.

.

MAINTENANCE OF GENERAL ANESTHESIA

A. Intermittent Propofol Injections:
Anesthesia can be maintained by administering propofol in intermittent IV injections. Clinical response will be determined by the amount and the frequency of maintenance injections. The following table is provided for guidance:

Maintenance Dosage Guidelines
Preanesthetic | Propofol Maintenance Dose | Rate of Administration
 | mg/kg | Seconds | mg/kg/min | mL/kg/min
None | 2.2 | 10 - 30 | 4.4 - 13.2 | .044 - 1.32
Acepromazine | 1.6 | 10 - 30 | 3.2 - 9.6 | 0.32 - 0.96
Acepromazine / Oxymorphone | 1.8 | 10 - 30 | 3.6 - 10.8 | 0.36 - 1.08

Repeated maintenance doses of propofol do not result in increased recovery times or dosing intervals, indicating that the anesthetic effects of propofol are not cumulative.

B. Maintenance by Inhalant Anesthetics:
Due to the rapid metabolism of propofol, additional low doses of propofol, similar to those used for maintenance with propofol, may be required to complete the transition to inhalant maintenance anesthesia.

Clinical trials using propofol have shown that it may be necessary to use a higher initial concentration of the inhalant anesthetic halothane than is usually required following induction using barbiturate anesthetics, due to rapid recovery from propofol^5.

OVERDOSAGE

Rapid administration or accidental overdosage of propofol may cause cardiopulmonary depression. Respiratory arrest (apnea) may be observed. In cases of respiratory depression, stop drug administration, establish a patent airway, and initiate assisted or controlled ventilation with pure oxygen. Cardiovascular depression should be treated with plasma expanders, pressor agents, antiarrhythmic agents or other techniques as appropriate for the observed abnormality.

WARNINGS

Rapid single or repeat bolus administration may cause undesirable cardiorespiratory depression including hypotension, apnea and oxygen desaturation.

When using propofol, dogs should be continuously monitored and facilities for the maintenance of a patent airway, artificial ventilation, and oxygen supplementation must be immediately available.

SIDE EFFECTS

The primary side effect of propofol is respiratory depression as evidenced by tachypnea and apnea. Tachypnea and apnea were observed in 43 and 26% of the cases in the clinical trial, respectively. All cases of apnea resumed normal breathing spontaneously, or responded satisfactorily to oxygen supplementation and/or controlled ventilation.

Other transient side effects are observed infrequently or rarely:
Respiratory: labored breathing
Cardiovascular: hypotension, bradycardia, tachycardia, membrane cyanosis, arrhythmias
Musculoskeletal: fasciculations, tenseness, paddling, movements
Central Nervous System: excitation, opisthotonus, seizures, excessive depression
Gastrointestinal: emesis, retching, salivation

PRECAUTIONS

1. Propofol contains no antimicrobial preservatives. Strict aseptic techniques must always be maintained during handling since the vehicle is capable of supporting the rapid growth of microorganisms. Failure to follow aseptic handling procedures may result in microbial contamination causing fever, infection/sepsis, and/or other life-threatening illness. Do not use if contamination is suspected. Once propofol has been opened, vial contents should be drawn into sterile syringes; each syringe should be prepared for single patient use only. Unused product should be discarded within 6 hours.

2. Anesthesia effects: Careful monitoring of the patient is necessary when using propofol as a maintenance anesthetic due to the possibility of rapid arousal. Apnea may occur following maintenance doses of propofol. Following induction, additional propofol may be needed to complete the transition to inhalant maintenance anesthesia due to rapid recovery from propofol. Doses administered during the transition to inhalant anesthesia may result in apnea. Propofol has also been used during inhalant maintenance anesthesia to increase anesthetic depth. Propofol used during inhalant maintenance may result in apnea.

3. Physiological effects: Mild hypotension may occur during propofol anesthesia.

4. Premedicants: Premedicants may increase the anesthesia or sedative effect of propofol and result in more pronounced changes in systolic, diastolic and mean arterial blood pressures.

5. Breeding animals: The use of propofol in pregnant and breeding dogs has not been evaluated. Propofol crosses the placenta and, as with other general anesthetic agents, the administration of propofol may be associated with neonatal depression.

6. Neonates: Propofol has not been evaluated in dogs less than 10 weeks of age.

7. Compromised or debilitated dogs: Doses may need adjustment for geriatric or debilitated patients. The administration of propofol to patients with renal failure and/or hepatic failure has not been evaluated. As with other anesthetic agents, caution should be exercised in dogs with cardiac, respiratory, renal or hepatic impairment, or in hypovolemic or debilitated dogs. Geriatric dogs may require less propofol for induction of anesthesia (see Dosage and Administration).

8. Sighthounds: Propofol induction and maintenance produced satisfactory anesthesia and recoveries in sighthounds. In the clinical study, a total of 27 sighthounds were induced with propofol, 6 of which were maintained on propofol. Induction doses were similar in sighthounds compared to other animals, however, recoveries were delayed.

9. Cardiac arrhythmias: In one study, propofol increased myocardial sensitivity to the development of epinephrine-induced ventricular arrhythmias in a manner similar to other anesthetics.^6 In the clinical study, transient ventricular arrhythmias associated with propofol were observed in 2 of 145 animals induced and maintained on propofol.

10. Concurrent medication: No significant adverse interactions with commonly used drugs have been observed.

11. Perivascular administration: Perivascular administration does not produce local tissue reaction.

CONTRAINDICATIONS

Propofol injection is contraindicated in dogs with a known hypersensitivity to propofol or its components, or when general anesthesia or sedation are contraindicated.

HUMAN USER SAFETY

Not for human use. Keep out of the reach of children.

Rare cases of self-administration have been reported, including fatalities. Propofol should be managed to prevent the risk of diversion, through such measures as restriction of access and the use of drug accountability procedures appropriate to the clinical setting.

Exercise caution to avoid accidental self-injection. Overdose is likely to cause cardiorespiratory depression (such as hypotension, bradycardia and/ or apnea). Remove the individual from the source of exposure and seek medical attention. Respiratory depression should be treated by artificial ventilation and oxygen.

Hypersensitivity reactions to propofol, including anaphylaxis, may occur in some individuals who are also allergic to muscle relaxants^7.

Avoid inhalation and direct contact of this product with skin, eyes, and clothes. In case of contact, eyes and skin should be liberally flushed with water for 15 minutes. Consult a physician if irritation persists.

CONTACT INFORMATION

To report suspected adverse events, for technical assistance or to obtain a copy of the Safety Data Sheet (SDS) contact Zoetis Inc. at 1-888-963-8471. For additional information about adverse drug experience reporting for animal drugs, contact FDA at 1-888-FDA-VETS or online at www.fda.gov/reportanimalae.

STORAGE

Propofol undergoes oxidative degradation in the presence of oxygen and is therefore packaged under nitrogen to eliminate this degradation path. Store between 4 – 25°C (40-77°F). Do not freeze. Protect from light. Shake well before use.

HOW SUPPLIED

PropoFlo™ is supplied in cartons of five-20 mL (200 mg per vial) vials containing 10 mg propofol per mL.

REFERENCES

1. Detailed information on the pharmacokinetics and metabolism of propofol can be obtained from Zoetis Inc.

2. Smith, J.A., J.S. Gaynor, R.M. Bednarski and W.W. Muir. Adverse effects of administration of propofol with various preanesthetic regimens in dogs. JAVMA. 202:1111-1115 (1993).

3. Plumb, D.C. ed. Veterinary Drug Handbook, Second Edition. Iowa State University Press, Ames, IA (1995).

4. Detailed information on the preanesthetic doses used with propofol in clinical studies is available in the Freedom of Information (FOI) Summary or can be obtained from Zoetis Inc.

5. Muir, W.W., J.A.E. Hubbell, R.T. Skarda, and R.M. Bednarski. Handbook of Veterinary Medicine, Second Edition. Mosby-Year Book, Inc. (1995).

6. Kamibayashi, T., Y. Hayashi, K. Sumikawa, A. Yamatodani, K. Kawabata and I. Yoshiya. Enhancement by propofol of epinephrine-induced arrhythmias in dogs. Anesthesiology 75:1035-1040 (1991).

7. Laxenaire, M.C., E. Mata-Bermejo, D.A. Moneret-Vautrin and J.L. Gueant. Life-threatening anaphylactoid reactions to propofol (Diprivan®). Anesthesiology 77:275-280 (1992).

Approved by FDA under NADA # 141-098
zoetis
Distributed by:
Zoetis Inc.
Kalamazoo, MI 49007
Revised: June 2022

339 708